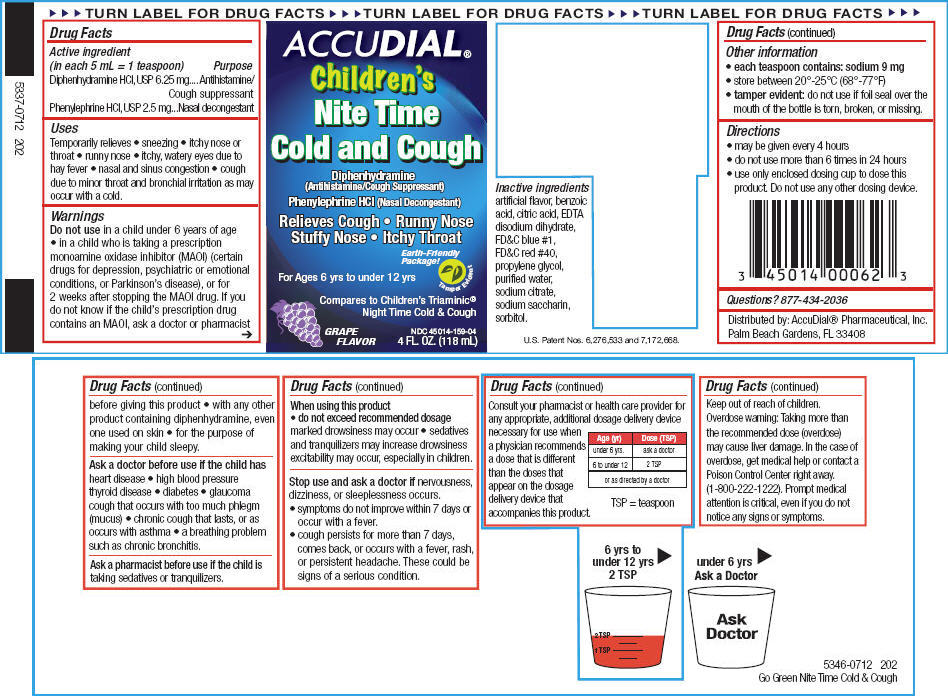 DRUG LABEL: Nite Time Cold and Cough
NDC: 45014-159 | Form: SOLUTION
Manufacturer: Accudial Pharmaceutical, Inc.
Category: otc | Type: HUMAN OTC DRUG LABEL
Date: 20130206

ACTIVE INGREDIENTS: Diphenhydramine Hydrochloride 6.25 mg/5 mL; Phenylephrine Hydrochloride 2.5 mg/5 mL
INACTIVE INGREDIENTS: Benzoic Acid; Citric Acid Monohydrate; Edetate Disodium; FD&C Blue No. 1; FD&C Red No. 40; Propylene Glycol; Water; Sodium Citrate; Saccharin Sodium; Sorbitol

Nite Time Cold & Cough

Drug Facts

ACTIVE INGREDIENT

Active ingredient (in each 5 mL = 1 teaspoon) | Purpose
Diphenhydramine HCl, USP 6.25 mg | Antihistamine/Cough suppressant
Phenylephrine HCl, USP 2.5 mg | Nasal decongestant

Uses

Temporarily relieves

- sneezing
- itchy nose or throat
- runny nose
- itchy, watery eyes due to hay fever
- nasal and sinus congestion
- cough due to minor throat and bronchial irritation as may occur with a cold.

Warnings

Do not use in a child under 6 years of age

- in a child who is taking a prescription monoamine oxidase inhibitor (MAOI) (certain drugs for depression, psychiatric or emotional conditions, or Parkinson's disease), or for 2 weeks after stopping the MAOI drug. If you do not know if the child's prescription drug contains an MAOI, ask a doctor or pharmacist before giving this product
- with any other product containing diphenhydramine, even one used on skin
- for the purpose of making your child sleepy.

Ask a doctor before use if the child has heart disease

- high blood pressure thyroid disease
- diabetes
- glaucoma cough that occurs with too much phlegm (mucus)
- chronic cough that lasts, or as occurs with asthma
- a breathing problem such as chronic bronchitis.

ASK DOCTOR/PHARMACIST

Ask a pharmacist before use if the child is taking sedatives or tranquilizers.

When using this product

- do not exceed recommended dosage marked drowsiness may occur
- sedatives and tranquilizers may increase drowsiness excitability may occur, especially in children.

Stop use and ask a doctor if nervousness, dizziness, or sleeplessness occurs.

- symptoms do not improve within 7 days or occur with a fever.
- cough persists for more than 7 days, comes back, or occurs with a fever, rash, or persistent headache. These could be signs of a serious condition.

ASK DOCTOR/PHARMACIST

Consult your pharmacist or health care provider for any appropriate, additional dosage delivery device necessary for use when a physician recommends a dose that is different than the doses that appear on the dosage delivery device that accompanies this product.

Age (yr) | Dose (TSP)
under 6 yrs. | ask a doctor
6 to under 12 | 2 TSP
or as directed by a doctor
TSP = teaspoon

Keep out of reach of children.

Overdose warning

Taking more than the recommended dose (overdose) may cause liver damage. In the case of overdose, get medical help or contact a Poison Control Center right away. (1-800-222-1222). Prompt medical attention is critical, even if you do not notice any signs or symptoms.

Other information

- each teaspoon contains: sodium 9 mg
- store between 20°-25°C (68°-77°F)
- tamper evident: do not use if foil seal over the mouth of the bottle is torn, broken, or missing.

Directions

- may be given every 4 hours
- do not use more than 6 times in 24 hours
- use only enclosed dosing cup to dose this product. Do not use any other dosing device.

Inactive ingredients

artificial flavor, benzoic acid, citric acid, EDTA disodium dihydrate, FD&C blue #1, FD&C red #40, propylene glycol, purified water, sodium citrate, sodium saccharin, sorbitol.

Questions?

877-434-2036

Distributed by: AccuDial® Pharmaceutical, Inc.
Palm Beach Gardens, FL 33408

PRINCIPAL DISPLAY PANEL - 118 mL Bottle Label

ACCUDIAL®
Children's
Nite Time
Cold and Cough

Diphenhydramine
(Antihistamine/Cough Suppressant)

Phenylephrine HCl (Nasal Decongestant)

Relieves Cough • Runny Nose
Stuffy Nose • Itchy Throat

Earth-Friendly
Package!

For Ages 6 yrs to under 12 yrs

Tamper Evident

Compares to Children's Triaminic®
Night Time Cold & Cough

GRAPE
FLAVOR

NDC 45014-159-04
4 FL. OZ. (118 mL)